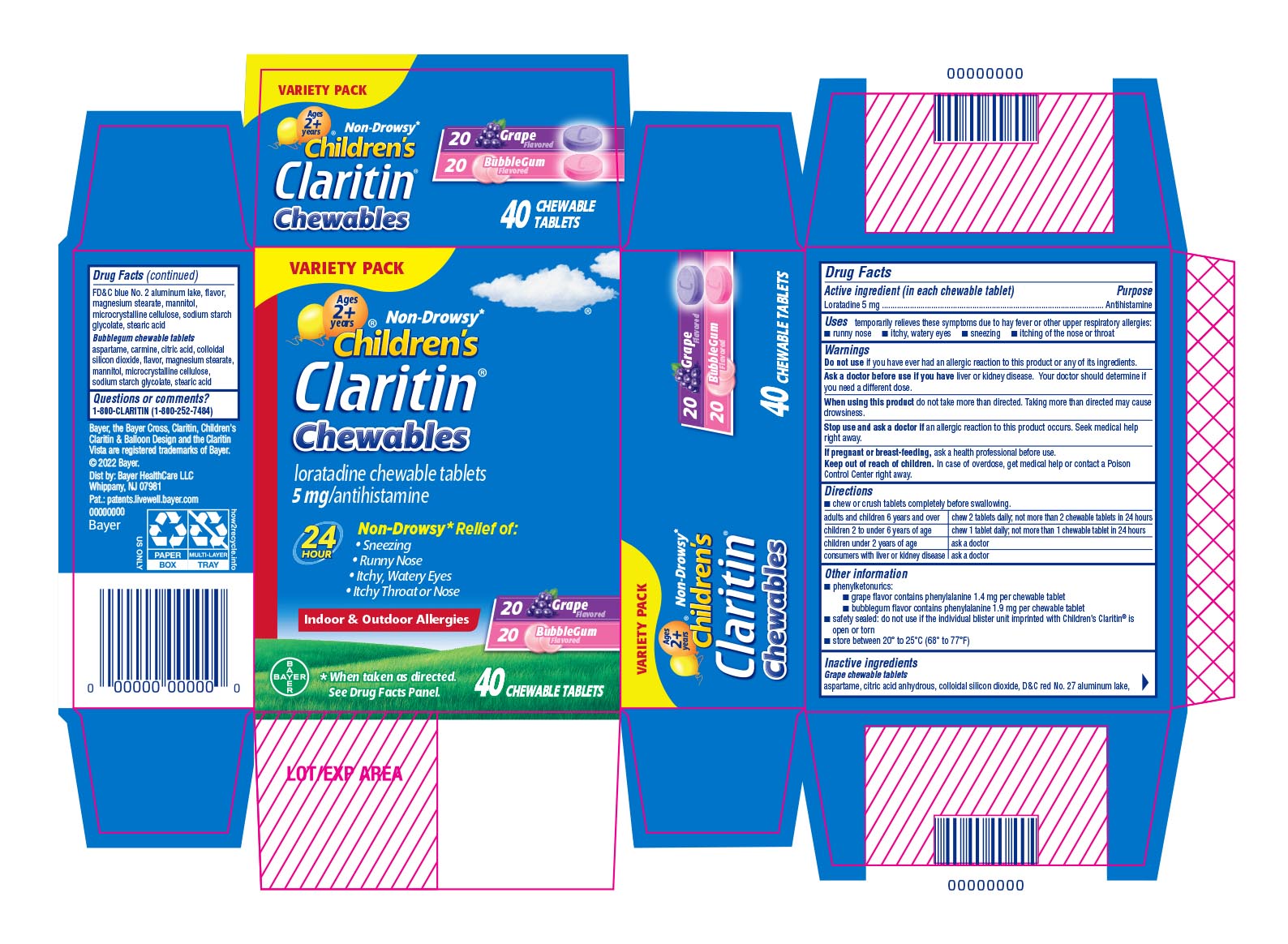 DRUG LABEL: Claritin Chewable Grape and Bubblegum
NDC: 11523-0123 | Form: KIT | Route: ORAL
Manufacturer: Bayer HealthCare LLC.
Category: otc | Type: HUMAN OTC DRUG LABEL
Date: 20251204

ACTIVE INGREDIENTS: LORATADINE 5 mg/1 1; LORATADINE 5 mg/1 1
INACTIVE INGREDIENTS: ASPARTAME; SILICON DIOXIDE; MAGNESIUM STEARATE; STEARIC ACID; ANHYDROUS CITRIC ACID; SODIUM STARCH GLYCOLATE TYPE A POTATO; D&C RED NO. 27; FD&C BLUE NO. 2; MANNITOL; CELLULOSE, MICROCRYSTALLINE; ASPARTAME; SILICON DIOXIDE; MAGNESIUM STEARATE; ANHYDROUS CITRIC ACID; SODIUM STARCH GLYCOLATE TYPE A POTATO; CARMINIC ACID; MANNITOL; CELLULOSE, MICROCRYSTALLINE; STEARIC ACID

Children's Claritin® Chewables 5mg Grape & Bubblegum UIs 1611948 & 1612741

Active ingredient (in each tablet)

Loratadine 5 mg

Purpose

Antihistamine

Uses

temporarily relieves these symptoms due to hay fever or other upper respiratory allergies:

●runny nose ●itchy, watery eyes ●sneezing ●itching of the nose or throat

Warnings

Do not use if you have ever had an allergic reaction to this product or any of its ingredients.

Ask a doctor before use if you have liver or kidney disease. Your doctor should determine if you need a different dose.

When using this product do not take more than directed. Taking more than directed may cause drowsiness.

Stop use and ask a doctor if an allergic reaction to this product occurs. Seek medical help right away.

PREGNANCY OR BREAST FEEDING

If pregnant or breast-feeding, ask a health professional before use.

Keep out of reach of children. In case of overdose, get medical help or contact a Poison Control Center right away.

Directions

- chew or crush tablets completely before swallowing.

adults and children 6 years and over | chew 2 tablets daily; not more than 2 chewable tablets in 24 hours
children 2 to under 6 years of age | chew 1 tablet daily; not more than 1 chewable tablet in 24 hours
children under 2 years of age | ask a doctor
consumers with liver or kidney disease | ask a doctor

Other Information

phenylketonurics:

- grape flavor contains phenylalanine 1.4 mg per chewable tablet
- bubblegum flavor contains phenylalanine 1.9 mg per chewable tablet

safety sealed: do not use if the individual blister unit imprinted with Children's Claritin® is open or torn
store between 20° to 25°C (68° to 77°F)

Inactive ingredients

Grape chewable tablets

aspartame, citric acid anhydrous, colloidal silicon dioxide, D&C red No. 27 aluminum lake, FD&C blue No. 2 aluminum lake, flavor, magnesium stearate, mannitol, microcrystalline cellulose, sodium starch glycolate, stearic aicd

Bubblegum chewable tablets

aspartame, carmine, citric acid, colloidal silicon dioxide, flavor, magnesium stearate, mannitol, microcrystalline cellulose, sodium starch glycolate, stearic acid

Questions or comments?

1-800-CLARITIN (1-800-252-7484)

PRINCIPAL DISPLAY PANEL - 40 Chewable Tablet Blister Pack Carton

VARIETY PACK

ages
2 +

years
Non-Drowsy*

Children's
Claritin ®

Chewables

loratadine chewable tablets

5 mg/antihistamine

24 Hour

Non-Drowsy* Relief of:

- Sneezing
- Runny Nose
- Itchy, Watery Eyes
- Itchy Throat or Nose

Indoor & Outdoor Allergies

20 Grape Flavored

20 Bubblegum Flavored

*When taken as directed. See Drug Facts Panel.

40 CHEWABLE TABLETS